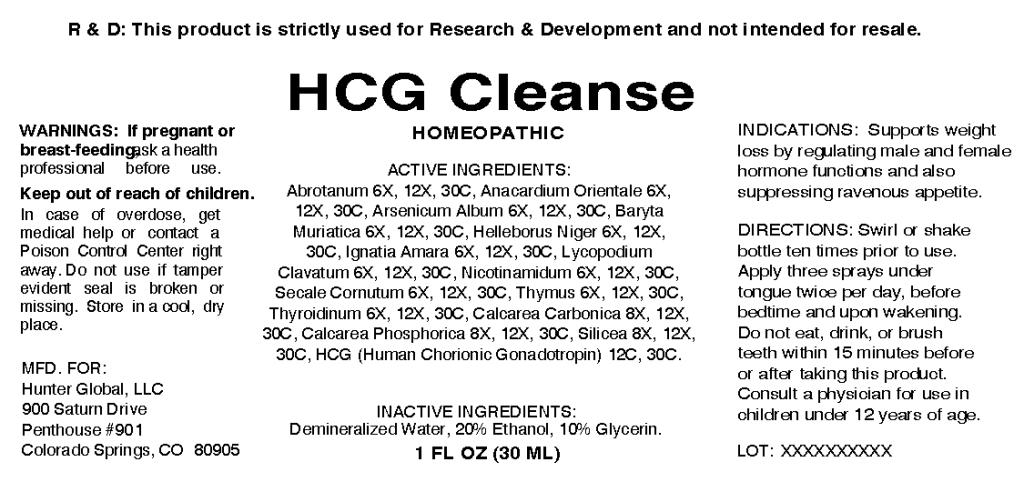 DRUG LABEL: HCG Cleanse
NDC: 57520-0502 | Form: SPRAY
Manufacturer: Apotheca Company
Category: homeopathic | Type: HUMAN OTC DRUG LABEL
Date: 20101022

ACTIVE INGREDIENTS: ARTEMISIA ABROTANUM FLOWERING TOP 30 [hp_C]/1 mL; SEMECARPUS ANACARDIUM JUICE 30 [hp_C]/1 mL; ARSENIC TRIOXIDE 30 [hp_C]/1 mL; BARIUM CHLORIDE DIHYDRATE 30 [hp_C]/1 mL; HELLEBORUS NIGER ROOT 30 [hp_C]/1 mL; STRYCHNOS IGNATII SEED 30 [hp_C]/1 mL; LYCOPODIUM CLAVATUM SPORE 30 [hp_C]/1 mL; NIACINAMIDE 30 [hp_C]/1 mL; CLAVICEPS PURPUREA SCLEROTIUM 30 [hp_C]/1 mL; SUS SCROFA THYMUS 30 [hp_C]/1 mL; SUS SCROFA THYROID 30 [hp_C]/1 mL; OYSTER SHELL CALCIUM CARBONATE, CRUDE 30 [hp_C]/1 mL; SILICON DIOXIDE 30 [hp_C]/1 mL; HUMAN CHORIONIC GONADOTROPIN 30 [hp_C]/1 mL; TRIBASIC CALCIUM PHOSPHATE 30 [hp_C]/1 mL
INACTIVE INGREDIENTS: WATER; ALCOHOL; GLYCERIN

HCG Cleanse

ACTIVE INGREDIENT

ACTIVE INGREDIENTS: Abrotanum 6X, 12X, 30C, Anacardium orientale 6X, 12X, 30C, Arsenicum album 6X, 12X, 30X, Baryta muriatica 6X, 12X, 30C, Helleborus niger 6X, 12X, 30C, Ignatia amara 6X, 12X, 30C, Lycopodium clavatum 6X, 12X, 30C, Nicotinamidum 6X, 12X, 30C, Secale cornutum 6X, 12X, 30C, Thymus 6X, 12X, 30C, Thyroidinum 6X, 12X, 30C, Calcarea carbonica 8X, 12X, 30C, Calcarea phosphorica 8X, 12X, 30C, Silicea 8X, 12X, 30X, HCG(Human chorionic gonadotropin) 12C, 30C.

PURPOSE

INDICATIONS: Supports weight loss by regulating male and female hormone functions and also suppressing ravenous appetite.

WARNINGS

WARNINGS: If pregnant or breast-feeding, ask a health professional before use.

Keep out of reach of children. In case of overdose, get medical help or contact a Poison Control Center right away.

Do not use if tamper evident seal is broken or missing. Store in a cool, dry place.

DOSAGE AND ADMINISTRATION

DIRECTIONS: Swirl or shake bottle ten times prior to use. Apply three sprays under tongue twice per day, before bedtime and upon wakening. Do not eat, drink, or brush teeth within 15 minutes before or after taking this product. Consult a physician for use in children under 12 years of age.

INACTIVE INGREDIENTS: Demineralized water, 20% Ethanol, 10% Glycerin.

KEEP OUT OF REACH OF CHILDREN: In case of overdose, get medical help or contact a Poison Control Center right away.

INDICATIONS AND USAGE

INDICATIONS: Supports weight loss by regulating male and female hormone functions and also suppressing ravenous appetite.

QUESTIONS

MFD. FOR:

Hunter Global, LLC

900 Saturn Drive

Penthouse #901

Colorado Springs, CO 80905

PACKAGE LABEL

R and D: This product is strictly used for Research and Development and not intended for resale

HCG CLEANSE

HOMEOPATHIC

1 FL OZ (30 ml)